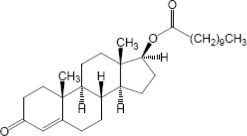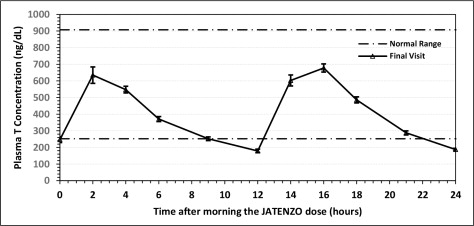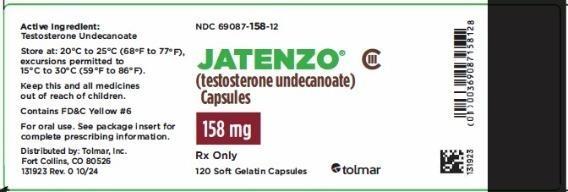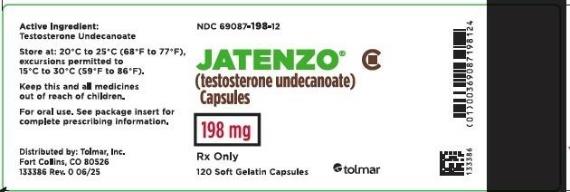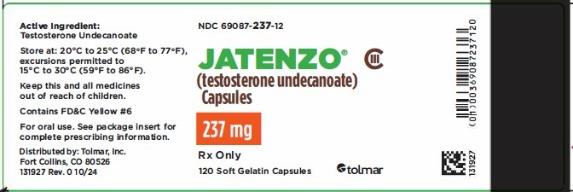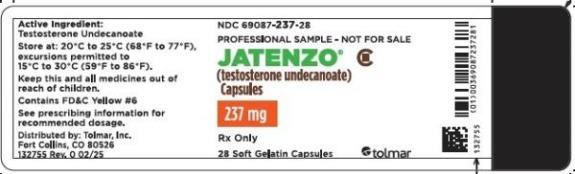 DRUG LABEL: Jatenzo
NDC: 69087-158 | Form: CAPSULE, LIQUID FILLED
Manufacturer: TOLMAR Inc.
Category: prescription | Type: HUMAN PRESCRIPTION DRUG LABEL
Date: 20250915
DEA Schedule: CIII

ACTIVE INGREDIENTS: TESTOSTERONE UNDECANOATE 158 mg/1 1
INACTIVE INGREDIENTS: OLEIC ACID; POLYOXYL 40 HYDROGENATED CASTOR OIL; BORAGE OIL; PEPPERMINT OIL; BUTYLATED HYDROXYTOLUENE; GELATIN; SORBITOL; GLYCERIN; WATER; FERRIC OXIDE RED; FD&C YELLOW NO. 6

HIGHLIGHTS OF PRESCRIBING INFORMATION

These highlights do not include all the information needed to use JATENZO® safely and effectively. See full prescribing information for JATENZO.
JATENZO (testosterone undecanoate) capsules, for oral use CIII
Initial U.S. Approval: 1953

RECENT MAJOR CHANGES

Boxed Warning, Increases in Blood Pressure Removed 07/2025

Indications and Usage (1) 07/2025

Contraindications, Men with “age related hypogonadism” (4) Removed 07/2025

Warnings and Precautions, Venous Thromboembolism (5.2) 07/2025

Warnings and Precautions, Blood Pressure Increases (5.4) 07/2025

Warnings and Precautions, Cardiovascular Risk (5.3) Removed 07/2025

1 INDICATIONS AND USAGE

JATENZO (testosterone undecanoate) is an androgen indicated for testosterone replacement therapy in adult males for conditions associated with a deficiency or absence of endogenous testosterone (1).

Limitations of use:

- Safety and efficacy of JATENZO in men with “age-related hypogonadism” have not been established (1)
- Safety and efficacy of JATENZO in males less than 18 years old have not been established (1, 8.4).

2 DOSAGE AND ADMINISTRATION

- Prior to initiating JATENZO, confirm the diagnosis of hypogonadism by ensuring that serum testosterone concentrations have been measured in the morning on at least two separate days and that these concentrations are below the normal range (2.1).
- Take JATENZO with food (2.2).
- Starting dose: 237 mg orally once in the morning and once in the evening.
- Adjust the dose to a minimum of 158 mg twice daily and a maximum of 396 mg twice daily based on serum testosterone drawn 6 hours after the morning dose at least 7 days after starting treatment or following dose adjustment and periodically thereafter (2.2).

3 DOSAGE FORMS AND STRENGTHS

JATENZO (testosterone undecanoate) capsules for oral use are available in the following strengths: 158 mg, 198 mg, 237 mg (3).

4 CONTRAINDICATIONS

- Men with breast cancer or known or suspected prostate cancer (4, 5.3).
- Women who are pregnant. Testosterone may cause fetal harm (4, 5.6, 8.1, 8.2).
- Known hypersensitivity to JATENZO or any of its ingredients (4).

5 WARNINGS AND PRECAUTIONS

- Polycythemia: Monitor hematocrit approximately every 3 months to detect increased red blood cell mass and polycythemia (5.1).
- Venous thromboembolism (VTE): VTE, including deep vein thrombosis (DVT) and pulmonary embolism (PE), have been reported in patients using testosterone. Evaluate patients with signs or symptoms consistent with DVT or PE (5.2).
- Worsening of Benign Prostatic Hyperplasia (BPH) and Potential Risk of Prostate Cancer: Monitor patients with benign prostatic hyperplasia (BPH) for worsening of signs and symptoms of BPH (5.3).
- Blood Pressure Increases: JATENZO can increase blood pressure, which can increase cardiovascular risk over time. Measure blood pressure periodically. Not recommended for use in men with uncontrolled hypertension (5.4)
- Abuse of Testosterone: Testosterone has been subject to abuse, typically at doses higher than recommended for the approved indication and in combination with other anabolic androgenic steroids (5.5).
- Potential for Adverse Effects on Spermatogenesis: Exogenous administration of androgens may lead to azoospermia (5.7).
- Edema: Edema, with or without congestive heart failure, may occur in patients with pre-existing cardiac, renal, or hepatic disease (5.9, 6.1).
- Sleep Apnea: Sleep apnea may occur in those with risk factors (5.11).
- Monitor prostate specific antigen (PSA) and lipid concentrations periodically (5.3, 5.12).
- Risk of Depression and Suicide: Depression and suicidal ideation have occurred during clinical trials in patients treated with JATENZO (5.15).

6 ADVERSE REACTIONS

Most common adverse reactions (incidence > 2%): polycythemia, diarrhea, dyspepsia, eructation, peripheral edema, nausea, increased hematocrit, headache, prostatomegaly, and hypertension (6.1).

To report SUSPECTED ADVERSE REACTIONS, contact Tolmar, Inc. at 1-844-4TO-LMAR or FDA at 1-800-FDA-1088 or www.fda.gov/medwatch.

7 DRUG INTERACTIONS

- Androgens may decrease blood glucose and therefore may decrease insulin requirements in diabetic patients (7.1).
- Changes in anticoagulant activity may be seen with androgens. More frequent monitoring of International Normalized Ratio (INR) and prothrombin time is recommended in patients taking warfarin (7.2).
- Use of testosterone with corticosteroids may result in increased fluid retention. Use with caution, particularly in patients with cardiac, renal, or hepatic disease (7.3).
- Concomitant administration of medications that are known to increase blood pressure may lead to additional increases in blood pressure when used with JATENZO (7.4).

8 USE IN SPECIFIC POPULATIONS

- Geriatric Patients: There are insufficient long-term safety data to assess the potential risks of cardiovascular disease and prostate cancer (8.5).

FULL PRESCRIBING INFORMATION

RECENT MAJOR CHANGES

Boxed Warning, Increases in Blood Pressure Removed 03/2025

Indications and Usage (1) 03/2025

Contraindications, Men with “age related hypogonadism” (4) Removed 03/2025

Warnings and Precautions , Venous Thromboembolism (5.2) 03/2025

Warnings and Precautions, Blood Pressure Increases (5.4) 03/2025

Warnings and Precautions, Cardiovascular Risk (5.3) Removed 03/2025

1 INDICATIONS AND USAGE

JATENZO (testosterone undecanoate) is an androgen indicated for testosterone replacement therapy in adult males for conditions associated with a deficiency or absence of endogenous testosterone:

- Primary hypogonadism (congenital or acquired): testicular failure due to conditions such as cryptorchidism, bilateral torsion, orchitis, vanishing testis syndrome, orchiectomy, Klinefelter syndrome, chemotherapy, or toxic damage from alcohol or heavy metals. These men usually have low serum testosterone concentrations and gonadotropins (follicle-stimulating hormone [FSH], luteinizing hormone [LH]) above the normal range.
- Hypogonadotropic hypogonadism (congenital or acquired): gonadotropin or luteinizing hormone-releasing hormone (LHRH) deficiency or pituitary-hypothalamic injury from tumors, trauma, or radiation. These men have low testosterone serum concentrations but have gonadotropins in the normal or low range.

Limitations of use:

- Safety and efficacy of JATENZO in men with “age-related hypogonadism” have not been established.
- Safety and efficacy of JATENZO in males less than 18 years old have not been established [see Use in Specific Populations (8.4)].

2 DOSAGE AND ADMINISTRATION

2.1 Confirmation of Hypogonadism Before Initiation of JATENZO

Prior to initiating JATENZO, confirm the diagnosis of hypogonadism by ensuring that serum testosterone concentrations have been measured in the morning on at least two separate days and that these testosterone concentrations are below the normal range.

2.2 Dosing and Dose Adjustment Information

Individualize the dosage of JATENZO based on the patient's serum testosterone concentration response to the drug. The recommended starting dose is 237 mg taken orally twice daily, once in the morning and once in the evening. Take JATENZO with food.

Dose Adjustment

To ensure proper dose adjustment, measure serum testosterone concentrations 6 hours after the morning dose in plain tubes, clotted at room temperature for 30 minutes prior to centrifugation. Adjust the JATENZO dose based on this serum testosterone measurement as shown in Table 1. Wait seven days after starting treatment or adjusting the dose before checking the serum testosterone concentration. Thereafter, periodically monitor serum testosterone concentrations 6 hours after the morning dose.

Administer the same dose in the morning and evening. The minimum recommended dose is 158 mg twice daily. The maximum recommended dose is 396 mg (two 198 mg capsules) twice daily.

Table 1: JATENZO Dose Adjustment Scheme
Testosterone Concentration in Serum From Plain Tube Drawn 6 hours After Morning Dose | Current JATENZO Dose (mg, twice daily) | New JATENZO Dose (mg, twice daily)
Less than 425 ng/dL | 158 | 198
Less than 425 ng/dL | 198 | 237
Less than 425 ng/dL | 237 | 316 (two 158 mg capsules)
Less than 425 ng/dL | 316 (two 158 mg capsules) | 396 (two 198 mg capsules)
425 ng/dL – 970 ng/dL | No Dose Change
More than 970 ng/dL | 396 (two 198 mg capsules) | 316 (two 158 mg capsules)
More than 970 ng/dL | 316 (two 158 mg capsules) | 237
More than 970 ng/dL | 237 | 198
More than 970 ng/dL | 198 | 158
More than 970 ng/dL | 158 | Discontinue Treatment

3 DOSAGE FORMS AND STRENGTHS

JATENZO capsules for oral use are available in three strengths:

- The 158 mg testosterone undecanoate capsules are opaque red and imprinted with “158” in white ink.
- The 198 mg testosterone undecanoate capsules are opaque white and imprinted with “198” in red ink.
- The 237 mg testosterone undecanoate capsules are opaque orange and imprinted with “237” in white ink.

4 CONTRAINDICATIONS

JATENZO is contraindicated in:

- Men with carcinoma of the breast or known or suspected carcinoma of the prostate [see Warnings and Precautions (5.3)].
- Women who are pregnant. Testosterone can cause virilization of the female fetus when administered to a pregnant woman [see Use in Specific Populations (8.1)].
- Men with known hypersensitivity to JATENZO or any of its ingredients [see Description (11)].

5 WARNINGS AND PRECAUTIONS

5.1 Polycythemia

Increases in hematocrit reflective of increases in red blood cell mass, may require lowering the dose or discontinuation of JATENZO. Check that hematocrit is not elevated prior to initiating JATENZO. Evaluate hematocrit approximately every 3 months while the patient is on JATENZO. If hematocrit becomes elevated, stop JATENZO until the hematocrit decreases to an acceptable concentration. If JATENZO is restarted and again causes hematocrit to become elevated, stop JATENZO permanently. An increase in red blood cell mass may increase the risk of thromboembolic events [see Warnings and Precautions (5.2)].

5.2 Venous Thromboembolism

There have been postmarketing reports of venous thromboembolic events, including deep vein thrombosis (DVT) and pulmonary embolism (PE), in patients using testosterone replacement products such as JATENZO.

In the Testosterone Replacement therapy for Assessment of long-term Vascular Events and efficacy ResponSE in hypogonadal men (TRAVERSE) Study, a randomized, double-blind, placebo-controlled, cardiovascular (CV) outcomes study, compared to placebo, topical testosterone gel was associated with a numerically higher incidence of VTE (1.7% vs 1.2%) which included DVT (0.6% vs 0.5%) and PE events (0.9% vs 0.5%) [see Adverse Reactions (6.1)].

Evaluate patients who report symptoms of pain, edema, warmth and erythema in the lower extremity for DVT and those who present with acute shortness of breath for PE. If a venous thromboembolic event is suspected, discontinue treatment with JATENZO and initiate appropriate workup and management [see Adverse Reactions (6.2)].

5.3 Worsening of Benign Prostatic Hyperplasia (BPH) and Potential Risk of Prostate Cancer

Patients with BPH treated with androgens are at an increased risk for worsening of signs and symptoms of BPH. Monitor patients with BPH for worsening signs and symptoms.

Patients treated with androgens may be at increased risk for prostate cancer. Evaluate patients for prostate cancer prior to initiating and during treatment with androgens [see Contraindications (4)].

5.4 Blood Pressure Increases

JATENZO can increase blood pressure. Ambulatory blood pressure monitoring (ABPM) demonstrated JATENZO increased systolic /diastolic BP by an average of 4.9/2.5 mm Hg from baseline after 4 months of treatment in a clinical trial [see Adverse Reactions (6.1)]. In patients with hypertension on antihypertensive therapy, JATENZO increased the mean systolic/diastolic BP by 5.4/3.2 mm Hg from baseline. Average blood pressures had not plateaued at the end of the trial.

The CV risk associated with topical testosterone gel was evaluated in TRAVERSE, a randomized, double-blind, placebo-controlled, CV outcomes study in men with a history of CV disease or multiple CV risk factors. In TRAVERSE, topical testosterone gel increased mean systolic blood pressure by 1.0 mm Hg from baseline to 36 months, whereas a mean decrease from baseline of 0.5 mm Hg was observed in the placebo group at this timepoint, for a mean between-group difference of 1.5 mm Hg. However, the incidences of major adverse cardiovascular events (MACE), including cardiovascular death, non-fatal myocardial infarction [MI] and non-fatal stroke, were similar between treatment groups (7% for topical testosterone gel vs 7.3% for placebo) [See Adverse Reactions (6.1)].

Monitor blood pressure periodically in men using JATENZO, especially men with hypertension. JATENZO is not recommended for use in patients with uncontrolled hypertension.

5.5 Abuse of Testosterone and Monitoring of Testosterone Concentrations

Testosterone has been subject to abuse, typically at doses higher than recommended for the approved indication and in combination with other anabolic androgenic steroids. Anabolic androgenic steroid abuse can lead to serious cardiovascular and psychiatric adverse reactions [see Drug Abuse and Dependence (9)].

If testosterone abuse is suspected, check testosterone concentrations to ensure they are within therapeutic range [see Dosage and Administration (2)]. However, testosterone levels may be in the normal or subnormal range in men abusing synthetic testosterone derivatives. Counsel patients concerning the serious adverse reactions associated with abuse of testosterone and anabolic androgenic steroids. Conversely, consider the possibility of testosterone and anabolic androgenic steroid abuse in suspected patients who present with serious cardiovascular or psychiatric adverse events.

5.6 Not for Use in Women

Due to lack of controlled studies in women and potential virilizing effects, JATENZO is not indicated for use in women [see Contraindications (4) and Use in Specific Populations (8.1, 8.2)].

5.7 Potential for Adverse Effects on Spermatogenesis

With large doses of exogenous androgens, including JATENZO, spermatogenesis may be suppressed through feedback inhibition of pituitary FSH possibly leading to adverse effects on semen parameters including sperm count [see Use in Specific Populations (8.3)]. Patients should be informed of this possible risk when deciding whether to use or to continue to use JATENZO.

5.8 Hepatic Adverse Effects

Prolonged use of high doses of orally active 17-alpha-alkyl androgens (e.g., methyltestosterone) has been associated with serious hepatic adverse effects (peliosis hepatis, hepatic neoplasms, cholestatic hepatitis, and jaundice). Peliosis hepatis can be a life-threatening or fatal complication. Long-term therapy with intramuscular testosterone enanthate has produced multiple hepatic adenomas. JATENZO is not known to cause these adverse effects. Nonetheless, patients should be instructed to report any signs or symptoms of hepatic dysfunction (e.g. jaundice). If these occur, promptly discontinue JATENZO while the cause is evaluated.

5.9 Edema

Androgens, including JATENZO, may promote retention of sodium and water. Edema, with or without congestive heart failure, may be a serious complication in patients with pre-existing cardiac, renal, or hepatic disease. In addition to discontinuation of the drug, diuretic therapy may be required.

5.10 Gynecomastia

Gynecomastia may develop and persist in patients being treated for hypogonadism.

5.11 Sleep Apnea

The treatment of hypogonadal men with testosterone may potentiate sleep apnea in some patients, especially those with risk factors such as obesity or chronic lung disease.

5.12 Lipid Changes

Changes in the serum lipid profile may require dose adjustment of lipid lowering drugs or discontinuation of testosterone therapy. Monitor the lipid profile periodically, particularly after starting testosterone therapy.

5.13 Hypercalcemia

Androgens, including JATENZO, should be used with caution in cancer patients at risk of hypercalcemia (and associated hypercalciuria). Monitor serum calcium concentrations regularly during treatment with JATENZO in these patients.

5.14 Decreased Thyroxine-binding Globulin

Androgens, including JATENZO, may decrease concentrations of thyroxin-binding globulin, resulting in decreased total T4 serum concentrations and increased resin uptake of T3 and T4. Free thyroid hormone concentrations remain unchanged, however, and there is no clinical evidence of thyroid dysfunction.

5.15 Risk of Depression and Suicide

Depression and suicidal ideation has been reported in patients treated with JATENZO in clinical trials. Advise patients and caregivers to seek medical attention for manifestations of new onset or worsening depression, suicidal ideation or behavior, anxiety, or other mood changes [see Adverse Events (6.1)].

6 ADVERSE REACTIONS

6.1 Clinical Trial Experience

Because clinical trials are conducted under widely varying conditions, adverse reaction rates observed in the clinical trials of a drug cannot be directly compared to rates in the clinical trials of another drug and may not reflect the rates observed in practice.

The safety of JATENZO was evaluated in a randomized, controlled clinical study with 166 patients treated with JATENZO twice daily with morning and evening meals for approximately 4 months. All patients were started on 237 mg twice daily, then the dose was titrated to 158 mg, 198 mg, 316 mg, or 396 mg twice daily to achieve testosterone concentrations in the eugonadal range.

Table 2 summarizes adverse reactions (≥2%) reported in this 4-month study.

Table 2: Number (%) of Patients with Adverse Reactions ≥ 2% in a 4-Month Study with JATENZO
Preferred Term | Overall (N = 166) n (%)
Headache | 8 (4.8)
Hematocrit increased | 8 (4.8)
Hypertension | 6 (3.6)
High-density lipoprotein decreased | 5 (3.0)
Nausea | 4 (2.4)
Among the 569 patients who received JATENZO in all Phase 2 and 3 trials combined, the following adverse reactions were reported in >2% of patients: polycythemia, diarrhea, dyspepsia, eructation, peripheral edema, nausea, increased hematocrit, headache, prostatomegaly, and hypertension.
Three of the 166 patients (1.8%) in the 4-month study experienced adverse reactions that led to premature discontinuation from the study, including rash (n=1) and headache (n=2).

BP Increases

In the 4-month clinical study, 24-hour ABPM was conducted on 166 patients. ABPM was conducted at baseline and at Day 139 of JATENZO therapy. A total of 135 patients had acceptable ABPM recordings at both time periods and were at least 85% compliant with study drug. In that group, the mean change in 24-hour systolic BP and diastolic BP from baseline to final on-treatment visit on Day 139 (n=135) was +4.9 mm Hg (95% CI 3.5, 6.4) and +2.5 mm Hg (95% CI 1.5, 3.6), respectively.

In patients with a history of hypertension who were receiving antihypertensive therapy, the mean ABPM systolic and diastolic BP increased by 5.4 mm Hg [95% CI 3.3, 7.6] and 3.2 mm Hg [95% CI 1.7, 4.7], respectively [n=67]. In patients with no history of hypertension, the mean ABPM systolic and diastolic blood pressure increased by 4.4 mm Hg [95% CI 2.3, 6.4] and 1.8 mm Hg [95% CI 0.2, 3.3], respectively [n=63].

Twelve (7.2%) patients on JATENZO either started antihypertensive medications or had their antihypertensive regimen increased during the study.

A total of 6 patients were reported to have an adverse reaction of hypertension (2 patients with hypertension and 4 patients with worsening hypertension), and 3 were reported to have an adverse reaction of increased blood pressure.

HR Increases

JATENZO increased mean heart rate by an average of 2.2 beats per minute (bpm) [95% CI (1.0, 3.3), N=135] during the study. Patients without a history of hypertension had a greater average increase in mean heart rate (2.7 bpm [95% CI (0.8, 4.6), N=63]) compared to patients with treated hypertension (1.9 bpm [95% CI (0.3, 3.5), N=67)]).

Increases in Hematocrit

Increases in hematocrit were reported in 8 of the 166 (4.8%) patients, which occurred in the second half of the study. None of these increases led to premature discontinuation of JATENZO.

Headaches

Headaches were reported in 8 of the 166 patients (4.8%) of which three required treatment with analgesics or non-steroidal anti-inflammatory drugs and 2 led to premature discontinuation from the study. Five of these 8 patients had headache events that resolved within 1 to 2 days.

Depression and suicidal ideation

Two of the 166 patients (1.2%) reported either worsening depression (n=1) or new-onset depression (n=1). One of the 569 patients (0.2%) in clinical trials had suicidal ideation. Each patient completed the study.

Increases in Serum PSA

The mean increase from baseline in PSA was 0.2 ng/mL (n=161). Increases in serum PSA concentrations, defined as an increase from baseline of at least 1.4 ng/mL or PSA greater than 4 ng/mL, occurred in 3 (1.9%) of the patients at the final visit.

Cardiovascular Outcomes

TRAVERSE was a randomized, double-blind, cardiovascular outcomes study to assess the cardiovascular (CV) safety of topical testosterone gel compared to placebo in 5198 hypogonadal men aged 45 to 80 years with a history of CV disease or with multiple CV risk factors. The primary outcome was the incidence of the composite endpoint of major adverse cardiovascular events (MACE), consisting of CV death, non-fatal myocardial infarction (MI), and non-fatal stroke.

The mean duration of therapy was approximately 22 months. The mean duration of follow-up was 33 months. Approximately 61% of all patients discontinued topical testosterone gel or placebo therapy.

The mean patient age (±SD) was 63.3 (7.9) years, with 2452 patients aged 65 years or more (47%); 2847 (about 55%) patients had pre-existing cardiovascular disease, whereas 2357 patients (about 45%) had an elevated cardiovascular risk at baseline, and mean BMI was 35kg/m^2. Approximately 80% of patients were White, 17% were Black, and 3% were of other races or ethnic groups. Approximately 69%, 84%, and 93% had diabetes mellitus, hyperlipidemia, and hypertension, respectively.

The mean serum testosterone concentration at baseline in patients receiving topical testosterone gel was 220.4 ng/dL (n=2596). The mean serum testosterone concentrations at 12 months, 24 months, 36 months, and 48 months in patients receiving topical testosterone gel were 440.5 ng/dL (n=1683), 420.9 ng/dl (n=1125), 428.7 ng/dL (n=731), and 365.2 ng/dL (n=220), respectively.

For patients treated with topical testosterone gel, the incidence of MACE was 7.0% (n=182 events) and for those receiving placebo, the incidence of MACE was 7.3% (n=190 events). The study demonstrated non-inferiority of topical testosterone gel versus placebo because the upper bound of 95% CI was less than the pre-specified risk margin, of 1.5 for MACE (Hazard Ratio 0.96 [95% CI: 0.78, 1.17]).

Additional Adverse Reactions Reported in TRAVERSE

Additional adverse reactions reported in TRAVERSE at an incidence rate >2% in either treatment group and greater in topical testosterone gel versus placebo included: nonfatal arrythmias warranting intervention (5.2% vs 3.3%), atrial fibrillation (3.5% vs 2.4%), acute kidney injury (2.3% vs 1.5%) and bone fracture (3.5% vs 2.5%). For the adverse reaction of bone fracture, each event was adjudicated by clinical review.

6.2 Postmarketing Experience

The following adverse reactions have been identified during post-approval use of testosterone. Because these reactions are reported voluntarily from a population of uncertain size, it is not always possible to reliably estimate their frequency or establish a causal relationship to drug exposure.

Cardiovascular Disorders: myocardial infarction, stroke [see Warnings and Precautions (5.4), Clinical Trial Experience (6.1)]

Vascular Disorders: Venous thromboembolism [see Warnings and Precautions (5.1)]

7 DRUG INTERACTIONS

7.1 Insulin

Changes in insulin sensitivity or glycemic control may occur in patients treated with androgens. In diabetic patients, the metabolic effects of androgens may decrease blood glucose and, therefore, may necessitate a decrease in the dose of anti-diabetic medication.

7.2 Oral Vitamin K Antagonist Anticoagulants

Changes in anticoagulant activity may be seen with androgens; therefore, more frequent monitoring of international normalized ratio (INR) and prothrombin time are recommended in patients taking warfarin, especially at the initiation and termination of androgen therapy.

7.3 Corticosteroids

The concurrent use of testosterone with corticosteroids may result in increased fluid retention and requires careful monitoring particularly in patients with cardiac, renal or hepatic disease.

7.4 Medications that May Also Increase Blood Pressure

Some prescription medications and nonprescription analgesic and cold medications contain drugs known to increase blood pressure. Concomitant administration of these medications with JATENZO may lead to additional increases in blood pressure [see Warnings and Precautions (5.4)].

8 USE IN SPECIFIC POPULATIONS

8.1 Pregnancy

Risk Summary

JATENZO is contraindicated in pregnant women. Testosterone is teratogenic and may cause fetal harm based on data from animal studies and its mechanism of action [see Contraindications (4) and Clinical Pharmacology (12.1)]. Exposure of a female fetus to androgens may result in varying degrees of virilization. In animal developmental studies, exposure to testosterone in utero resulted in hormonal and behavioral changes in offspring and structural impairments of reproductive tissues in female and male offspring. These studies did not meet current standards for nonclinical development toxicity studies.

Data

Animal Data

In developmental studies conducted in rats, rabbits, pigs, sheep and rhesus monkeys, pregnant animals received intramuscular injection of testosterone during the period of organogenesis. Testosterone treatment at doses that were comparable to those used for testosterone replacement therapy resulted in structural impairments in both female and male offspring. Structural impairments observed in females included increased anogenital distance, phallus development, empty scrotum, no external vagina, intrauterine growth retardation, reduced ovarian reserve, and increased ovarian follicular recruitment. Structural impairments seen in male offspring included increased testicular weight, larger seminal tubular lumen diameter, and higher frequency of occluded tubule lumen. Increased pituitary weight was seen in both sexes.

Testosterone exposure in utero also resulted in hormonal and behavioral changes in offspring. Hypertension was observed in pregnant female rats and their offspring exposed to doses approximately twice those used for testosterone replacement therapy.

8.2 Lactation

Risk Summary

JATENZO is not indicated for use in women.

8.3 Females and Males of Reproductive Potential

Infertility

During treatment with large doses of exogenous androgens, including JATENZO, spermatogenesis may be suppressed through feedback inhibition of the hypothalamic-pituitary-testicular axis [see Warnings and Precautions (5.7)], possibly leading to adverse effects on semen parameters including sperm count. Reduced fertility is observed in some men taking testosterone replacement therapy. Testicular atrophy, subfertility, and infertility have also been reported in men who abuse anabolic androgenic steroids [see Drug Abuse and Dependence (9.2)]. With either type of use, the impact on fertility may be irreversible.

8.4 Pediatric Use

The safety and efficacy of JATENZO in pediatric patients less than 18 years old have not been established. Improper use may result in acceleration of bone age and premature closure of epiphyses.

8.5 Geriatric Use

There have not been sufficient numbers of geriatric patients involved in controlled clinical studies utilizing JATENZO to determine whether efficacy or safety in those over 65 years of age differs from younger subjects. No patients over 65 years of age were enrolled in the 4-month efficacy and safety clinical study utilizing JATENZO. Additionally, there is insufficient long-term safety data in geriatric patients utilizing JATENZO to assess the potentially increased risk of cardiovascular disease and prostate cancer.

Geriatric patients treated with androgens may also be at risk for worsening of signs and symptoms of BPH [see Warnings and Precautions (5.3)].

9 DRUG ABUSE AND DEPENDENCE

9.1 Controlled Substance

JATENZO contains testosterone undecanoate, which is a Schedule III controlled substance as defined under the Controlled Substances Act.

9.2 Abuse

Drug abuse is intentional non-therapeutic use of a drug, even once, for its rewarding psychological and physiological effects. Abuse and misuse of testosterone are seen in male and female adults and adolescents. Testosterone, often in combination with other anabolic androgenic steroids (AAS), and not obtained by prescription through a pharmacy, may be abused by athletes and bodybuilders. There have been reports of misuse by men taking higher doses of legally obtained testosterone than prescribed and continuing testosterone despite adverse events or against medical advice.

Abuse-Related Adverse Reactions

Serious adverse reactions have been reported in individuals who abuse anabolic androgenic steroids and include cardiac arrest, myocardial infarction, hypertrophic cardiomyopathy, congestive heart failure, cerebrovascular accident, hepatotoxicity, and serious psychiatric manifestations, including major depression, mania, paranoia, psychosis, delusions, hallucinations, hostility and aggression.

The following adverse reactions have also been reported in men: transient ischemic attacks, convulsions, hypomania, irritability, dyslipidemias, testicular atrophy, subfertility, and infertility.

The following additional adverse reactions have been reported in women: hirsutism, virilization, deepening of voice, clitoral enlargement, breast atrophy, male-pattern baldness, and menstrual irregularities.

The following adverse reactions have been reported in male and female adolescents: premature closure of bony epiphyses with termination of growth, and precocious puberty.

Because these reactions are reported voluntarily from a population of uncertain size and may include abuse of other agents, it is not always possible to reliably estimate their frequency or establish a causal relationship to drug exposure.

9.3 Dependence

Behaviors Associated with Addiction

Continued abuse of testosterone and other anabolic steroids, leading to addiction is characterized by the following behaviors:

- Taking greater dosages than prescribed
- Continued drug use despite medical and social problems due to drug use
- Spending significant time to obtain the drug when supplies of the drug are interrupted
- Giving a higher priority to drug use than other obligations
- Having difficulty in discontinuing the drug despite desires and attempts to do so
- Experiencing withdrawal symptoms upon abrupt discontinuation of use

Physical dependence is characterized by withdrawal symptoms after abrupt drug discontinuation or a significant dose reduction of a drug. Individuals taking supratherapeutic doses of testosterone may experience withdrawal symptoms lasting for weeks or months which include depressed mood, major depression, fatigue, craving, restlessness, irritability, anorexia, insomnia, decreased libido and hypogonadotropic hypogonadism.

Drug dependence in individuals using approved doses of testosterone for approved indications has not been documented.

10 OVERDOSAGE

There is a single report of acute overdosage with use of an approved injectable testosterone product: this subject had serum testosterone concentrations of up to 11,400 ng/dL which were implicated in a cerebrovascular accident.

One case of overdose with JATENZO was reported in clinical trials. This patient inadvertently took a higher dose than prescribed (474 mg twice daily, which is 20% higher than the maximum recommended dose). He did not report any adverse reactions associated with the overdose.

Treatment of overdosage consists of discontinuation of JATENZO and appropriate symptomatic and supportive care.

11 DESCRIPTION

JATENZO (testosterone undecanoate) for oral use is provided as a gelatin capsule containing testosterone undecanoate, a fatty-acid ester of testosterone. Testosterone undecanoate is a white to off-white yellow crystalline powder. Testosterone, an androgen, is formed by cleavage of the ester side chain of testosterone undecanoate.

Testosterone undecanoate is chemically described as 17β-hydroxyandrost-4-en-3-one undecanoate. It has the empirical formula of C30H48O3 and the molecular weight of 456.7. The structural formula for testosterone undecanoate is presented in Figure 1.

Figure 1: Testosterone Undecanoate

JATENZO capsules are available in three strengths of 158 mg, 198 mg, and 237 mg.

The 158 mg strength is an opaque red capsule that contains 158 mg of testosterone undecanoate and is imprinted with “158” in white ink. The 198 mg strength is an opaque white capsule that contains 198 mg of testosterone undecanoate and is imprinted with “198” in red ink. The 237 mg strength is an opaque orange capsule that contains 237 mg of testosterone undecanoate and is imprinted with “237” in white ink. All capsule strengths also contain oleic acid, polyoxyl 40 hydrogenated castor oil (Cremophor RH 40), borage seed oil, peppermint oil, and butylated hydroxytoluene as inactive ingredients.

Gelatin capsule shells are composed of the following inactive ingredients: Gelatin, sorbitol, glycerin, and purified water in all strengths, iron oxide red in 158 mg, FD&C Yellow #6 in 158 and 237 mg, and titanium dioxide in 198 and 237 mg capsules.

12 CLINICAL PHARMACOLOGY

12.1 Mechanism of Action

Endogenous androgens, including testosterone and dihydrotestosterone (DHT), are responsible for the normal growth and development of the male sex organs and for maintenance of secondary sex characteristics. These effects include the growth and maturation of prostate, seminal vesicles, penis and scrotum; the development of male hair distribution, such as facial, pubic, chest and axillary hair; laryngeal enlargement, vocal cord thickening, alterations in body musculature and fat distribution.

Male hypogonadism, a clinical syndrome resulting from insufficient secretion of testosterone, has two main etiologies. Primary hypogonadism is caused by defects of the gonads, such as Klinefelter syndrome or Leydig cell aplasia, whereas secondary hypogonadism (also known as hypogonadotropic hypogonadism) is the failure of the hypothalamus (or pituitary) to produce sufficient gonadotropins (FSH, LH).

12.2 Pharmacodynamics

No specific pharmacodynamic studies were conducted using JATENZO.

12.3 Pharmacokinetics

Absorption

JATENZO delivers physiologic amounts of testosterone, producing testosterone concentrations that approximate normal concentrations seen in healthy men.

JATENZO was taken orally at a starting dose of 237 mg twice per day with meals in a multicenter, open-label, randomized, 2-arm, active-controlled trial in hypogonadal males. The dose was adjusted, as needed, on Days 14 and 56 between a minimum of 158 mg twice per day and a maximum of 396 mg twice per day based on the average plasma testosterone concentration obtained over 24 hours after the morning dose. The average daily NaF-EDTA plasma testosterone concentration was 403 (± 128) ng/dL at the end of treatment, where the normal eugonadal range in NaF-EDTA plasma was 252-907 ng/dL in this study. Note that the titration scheme for use in clinical practice is based on serum total testosterone [see Dosage and Administration (2.2)].

Table 3 summarizes the pharmacokinetic (PK) parameters for plasma total testosterone in patients completing at least 105 days of JATENZO treatment administered twice daily.

Table 3: NaF-EDTA Plasma Testosterone Cavg and Cmax at Final PK Visit
PK Parameter |  | All Doses (N=151)
PK Parameter |  | All Doses (N=151)
Cavg (ng/dL) | Mean | 403
Cavg (ng/dL) | SD | 128
Cmax (ng/dL) | Mean | 1008
 | SD | 581
PK = pharmacokinetic; Cavg = 24-hour average concentration; Cmax = maximum concentration

Figure 2 summarizes the mean plasma total testosterone profile for the patients at the final PK visit.

Figure 2: Mean (±SEM) Concentration-Time Profile for NaF-EDTA Plasma Total Testosterone in JATENZO Treated Subjects at Final PK Visit

SEM = standard error of the mean; T = testosterone

When JATENZO was dosed with different breakfasts containing various amounts of fat, the bioavailability with the 30 g fat, 45 g fat, and high-calorie high-fat breakfasts was comparable, but there was a food effect with the 15 g fat breakfast compared to the 30 g fat breakfast. The 15 g fat breakfast had a 25% decrease in testosterone exposure compared to the 30 g fat breakfast.

Distribution

Circulating testosterone is primarily bound in serum to sex hormone-binding globulin (SHBG) and albumin. Approximately 40% of testosterone in plasma is bound to SHBG, 2% remains unbound (free) and the rest is loosely bound to albumin and other proteins.

Metabolism

The androgenic activity of testosterone undecanoate occurs after the ester bond linking the testosterone to the undecanoic acid is cleaved by endogenous non-specific esterases. Undecanoic acid is metabolized like all fatty acids via the beta-oxidation pathway.

Testosterone is metabolized to various 17-keto steroids through two different pathways. The major active metabolites of testosterone are dihydrotestosterone (DHT) and estradiol.

Drug Interaction Studies

Clinical Pharmacology Studies

Concomitant administration of JATENZO at 237 mg dose with midazolam (CYP3A4 substrate), digoxin (P-gp substrate), and rosuvastatin (BCRP substrate) had no clinically meaningful effect on the concentration of these substrates.

The potential for JATENZO doses higher than 237 mg to inhibit CYP3A4, P-gp and BCRP is unknown.

Excretion

About 90% of a dose of testosterone given intramuscularly is excreted in the urine as glucuronic and sulfuric acid conjugates of testosterone and its metabolites. About 6% of a dose is excreted in the feces, mostly in the unconjugated form. Inactivation of testosterone occurs primarily in the liver.

13 NONCLINICAL TOXICOLOGY

13.1 Carcinogenesis, Mutagenesis, Impairment of Fertility

Carcinogenesis

Testosterone has been tested by subcutaneous injection and implantation in mice and rats. In mice, the implant induced cervical-uterine tumors, which metastasized in some cases. There is suggestive evidence that injection of testosterone into some strains of female mice increases their susceptibility to hepatoma. Testosterone is also known to increase the number of tumors and decrease the degree of differentiation of chemically induced carcinomas of the liver in rats.

Mutagenesis

Testosterone was negative in the in vitro Ames and in the in vivo mouse micronucleus assays.

Impairment of Fertility

The administration of exogenous testosterone suppresses spermatogenesis in the rat, dog and non-human primates, which was reversible on cessation of the treatment.

13.2 Animal Toxicology and/or Pharmacology

JATENZO has been evaluated in 3- and 9-month repeat-dose oral toxicity studies in male eugonadal dogs. JATENZO caused exaggerated pharmacological effects on androgen-responsive tissues including testes, epididymis, prostate and adrenals at exposures to testosterone or testosterone undecanoate, comparable to the maximum human exposure based on AUC comparisons. Following a 4-week drug-free period, a reduced severity of these findings was observed, suggesting partial reversibility.

In adrenal glands, moderate to severe atrophy, characterized as thinning of the zona fasciculata, was observed with reduced adrenal weights and reduced circulating levels of cortisol in testosterone undecanoate-treated dogs after 3 months of treatment. Following 9-month treatment, there were dose-related decreases in adrenal weights in testosterone undecanoate-treated male dogs and moderate adrenal vacuolation in one testosterone undecanoate-treated male dog. The clinical significance of these adrenal and cortisol findings is unknown.

14 CLINICAL STUDIES

14.1 Clinical Trials in Hypogonadal Males

The efficacy and safety of JATENZO was evaluated in 166 adult hypogonadal males in an open-label study of approximately 4 months duration (NCT02722278). The study included a Screening Phase, a Treatment Titration Phase, and a Treatment Maintenance Phase.

JATENZO was taken orally at a starting dose of 237 mg twice per day with meals. The dose was adjusted on Days 21 and 56 between a minimum of 158 mg twice per day and a maximum of 396 mg twice per day on the basis of the average testosterone concentration obtained over 24 hours post-morning dose.

The primary endpoint was the percentage of patients with mean plasma total testosterone concentration (Cavg) over 24-hours within the normal eugonadal range on the final PK visit of the study.

Secondary endpoints were the percentage of patients with a maximum total testosterone concentration (Cmax) above three predetermined limits: less than or equal to 1500 ng/dL, between 1800 and 2500 ng/dL, and greater than 2500 ng/dL.

One hundred and forty-five (87%) of the 166 hypogonadal men who received JATENZO had a mean total testosterone concentration (Cavg) within the normal eugonadal range at the end of treatment.

The percentage of patients who received JATENZO and had Cmax less than or equal to 1500 ng/dL, between 1800 and 2500 ng/dL, and greater than 2500 ng/dL at the final PK visit were 83%, 3%, and 3%, respectively. Note that the testosterone concentrations were not measured in serum but the effects of different sample preparation conditions were accounted for in data analysis of the results shown here. The titration scheme for use in clinical practice is based on serum total testosterone [see Dosage and Administration (2.2)].

16 HOW SUPPLIED/STORAGE AND HANDLING

JATENZO (testosterone undecanoate) capsules are available in three strengths of 158 mg, 198 mg, and 237 mg. Capsules are packaged as 120 units in wide-mouth, round, white HDPE bottles with white, polypropylene, child resistant caps and induction-sealed liner.

158 mg capsules are opaque red capsules imprinted with “158” in white ink and are supplied in bottles: NDC 69087-158-12.

198 mg capsules are opaque white capsules imprinted with “198” in red ink and are supplied in bottles: NDC 69087-198-12.

237 mg capsules are opaque orange capsules imprinted with “237” in white ink and are supplied in bottles: NDC 69087-237-12.

Keep JATENZO out of reach of children.

Store at 20°C to 25ºC (68°F to 77ºF), excursions permitted to 15ºC to 30ºC (59ºF to 86ºF). Avoid exposing the capsules to moisture (store in a dry place).

17 PATIENT COUNSELING INFORMATION

Advise the patient to read the FDA-approved patient labeling (Medication Guide).

Venous Thromboembolism

- Inform patients that JATENZO can cause venous thromboembolism. Advise patients of the signs and symptoms of venous thromboembolism, which may include the following: lower limb pain, edema, or erythema; and dyspnea or chest pain. Advise patients to promptly report the signs and symptoms of venous thromboembolism, discontinue use of JATENZO, and seek urgent medical care.

Increased Blood Pressure

- Inform patients that JATENZO can increase BP which can increase cardiovascular risk over time.
- Instruct patients about the importance of monitoring BP periodically while on JATENZO. If BP increases while on JATENZO, antihypertensive medications may need to be started, added, or adjusted to control BP, or JATENZO may need to be discontinued.

Other Adverse Reactions

Inform patients that treatment with androgens may lead to adverse reactions which include:

- Changes in urinary habits related to effects on prostate size, such as increased urination at night, hesitancy, frequency, urinary urgency, having a urine accident, being unable to pass urine and weak urine flow
- Breathing disturbances that may reflect obstructive sleep apnea, including those associated with sleep, or excessive daytime sleepiness
- Too frequent or persistent erections of the penis
- Ankle swelling that may reflect peripheral edema
- Red blood cell count increase
- PSA increase
- Nausea and vomiting

Instruct patients to report any changes in their state of health, such as changes in urinary habits, breathing, sleep, and mood including new onset or worsening of depression, or suicidal ideation.

Keep JATENZO out of the reach of children.

Distributed by:
Tolmar, Inc. Fort Collins, CO 80526

133462 Rev. 1 09/2025

MEDICATION GUIDE
JATENZO® (juh-TEN-zoh)
(testosterone undecanoate) capsules, for oral use CIII

What is JATENZO?
JATENZO is a prescription medicine that contains testosterone. JATENZO is used to treat adult men who have low or no testosterone due to certain medical conditions.
It is not known if JATENZO is safe or effective to treat men who have low testosterone due to aging.
It is not known if JATENZO is safe or effective in children younger than 18 years old. Improper use of JATENZO may affect bone growth in children.

JATENZO is a controlled substance (CIII) because it contains testosterone that can be a target for people who abuse prescription medicines. Keep your JATENZO in a safe place to protect it. Never give your JATENZO to anyone else, even if they have the same symptoms you have. Selling or giving away this medicine may harm others and is against the law.
JATENZO is not meant for use by women.

Do not take JATENZO if you:

- have breast cancer.
- have or might have prostate cancer.
- are a woman who is pregnant. JATENZO may harm your unborn baby.
- are allergic to JATENZO or any ingredients in JATENZO. See the end of this Medication Guide for a complete list of ingredients in JATENZO.

Before you take JATENZO, tell your healthcare provider about all of your medical conditions, including if you:

- have high blood pressure or are treated for high blood pressure.
- have heart problems.
- have high red blood cell count (hematocrit) or high hemoglobin laboratory value.
- have urinary problems due to an enlarged prostate.
- have liver or kidney problems.
- have a history of mental health illness including suicidal thoughts or actions, depression, anxiety or mood disorder.
- have problems breathing while you sleep (sleep apnea).

Tell your healthcare provider about all the medicines you take, including prescription and over-the-counter medicines, vitamins, and herbal supplements.
Using JATENZO with certain other medicines can affect each other. Especially, tell your healthcare provider if you take:

- insulin
- medicines that decrease blood clotting (blood thinners)
- corticosteroids.
- medicines that increase blood pressure such as some cold medicines and pain medicines.

Know the medicines you take. Ask your healthcare provider or pharmacist for a list of these medicines, if you are not sure. Keep a list of them and show it to your healthcare provider and pharmacist when you get a new medicine.

How should I take JATENZO?

- Take JATENZO exactly as your healthcare provider tells you take it.
- Take JATENZO by mouth two times daily. Take 1 time in the morning and take 1 time in the evening.
- Take JATENZO with food.
- Your healthcare provider may change your JATENZO dose. Do not change your JATENZO dose without talking to your healthcare provider.

What are the possible side effects of JATENZO?
JATENZO may cause serious side effects including:

- Increase in blood pressure.
  - JATENZO can increase your blood pressure, which can increase your risk of having a heart attack or stroke over time. Your risk may be greater if you already have heart disease or if you have had a heart attack or stroke.
  - You may need to start new blood pressure medicines or have your medicines adjusted to control your blood pressure while on JATENZO.
  - If your blood pressure cannot be controlled, JATENZO may need to be stopped.
  - Your healthcare provider should check your blood pressure while you use JATENZO.
- Increase in red blood cell count (hematocrit) or hemoglobin.
  - JATENZO increases red blood cell counts in some patients. High red blood cell counts increase the risk of blood clots, strokes, and heart attacks.
  - You may need to stop JATENZO if your red blood cell count increases.
  - Your healthcare provider should check your red blood cell count and hemoglobin while you use JATENZO.
- If you already have an enlarged prostate, your signs and symptoms may worsen while using JATENZO.
  These may include:
  - increased urination at night
  - trouble starting your urine stream
  - urinating many times during the day
  - urge to go to the bathroom right away
  - a urine accident
  - inability to pass urine or weak urine flow
- Increased risk of prostate cancer. Your healthcare provider should check you for prostate cancer or any other prostate problems before you start and while you use JATENZO.
- Blood clots in the legs or lungs. Signs and symptoms of a blood clot in your leg can include pain, swelling or redness. Signs and symptoms of a blood clot in your lungs can include difficulty breathing or chest pain.
- Abuse. Testosterone can be abused, when taken at higher than prescribed doses and when used with other anabolic androgenic steroids. Abuse can cause serious heart and psychological side effects. Your healthcare provider should check you for signs of abuse before and during treatment with JATENZO.
- In large doses JATENZO may lower your sperm count.
- Liver problems. Symptoms of liver problems may include:
  - nausea or vomiting
  - yellowing of your skin or whites of your eyes
  - dark urine
  - pain on the right side of your stomach area (abdominal pain)
- Swelling of your ankles, feet, or body (edema), with or without heart failure.
- Enlarged or painful breasts.
- Breathing problems while you sleep (sleep apnea).
- Changes in mood. Talk to your healthcare provider if you have changes in mood or behavior including, new or worsening depression, or suicidal thoughts.

Call your healthcare provider right away if you have any of the serious side effects listed above.
The most common side effects of JATENZO include:

- increased red blood cell count
- diarrhea
- heart burn

- burping
- foot, leg and ankle swelling
- nausea

- enlarged prostate gland
- high blood pressure
- headache

Other side effects include more erections than are normal for you or erections that last a long time.
Tell your healthcare provider if you have any side effect that bothers you or that does not go away.
These are not all the possible side effects of JATENZO. For more information, ask your healthcare provider or pharmacist.
Call your doctor for medical advice about side effects. You may report side effects to FDA at 1-800-FDA-1088.

How should I store JATENZO?

- Store JATENZO at room temperature between 68°F to 77°F (20°C to 25°C).
- Store JATENZO in a dry place.

Keep JATENZO and all medicines out of the reach of children.

General information about the safe and effective use of JATENZO
Medicines are sometimes prescribed for purposes other than those listed in a Medication Guide. Do not use JATENZO for a condition for which it was not prescribed. Do not give JATENZO to other people, even if they have the same symptoms you have. It may harm them. You can ask your pharmacist or healthcare provider for information about JATENZO that is written for health professionals.

What are the ingredients in JATENZO?
Active ingredient: testosterone undecanoate
Inactive ingredients: oleic acid, polyoxyl 40 hydrogenated castor oil (Cremophor RH 40), borage seed oil, peppermint oil, and butylated hydroxytoluene. The ingredients of the soft gelatin capsule shells are gelatin, sorbitol, glycerin, purified water, iron oxide red, FD&C Yellow #6, and titanium dioxide.
Distributed by:
Tolmar, Inc. Fort Collins, CO 80526
For more information, go to www.JATENZO.com or call 1-844-4TO-LMAR.

This Medication Guide has been approved by the U.S. Food and Drug Administration

Issued: 09/2025